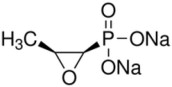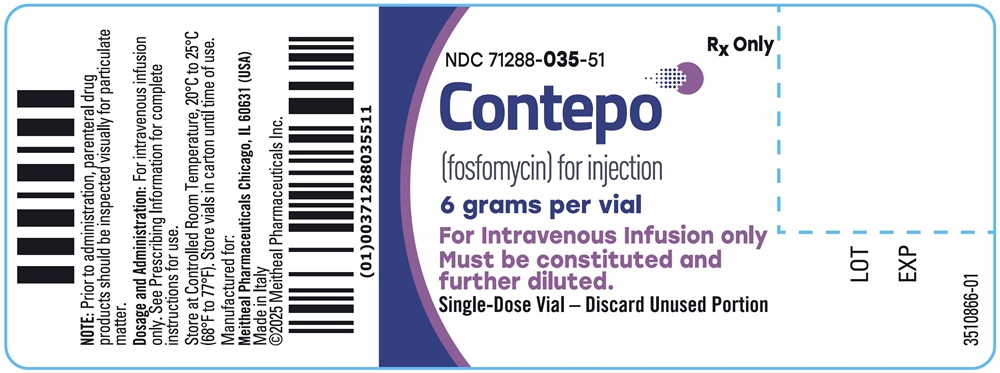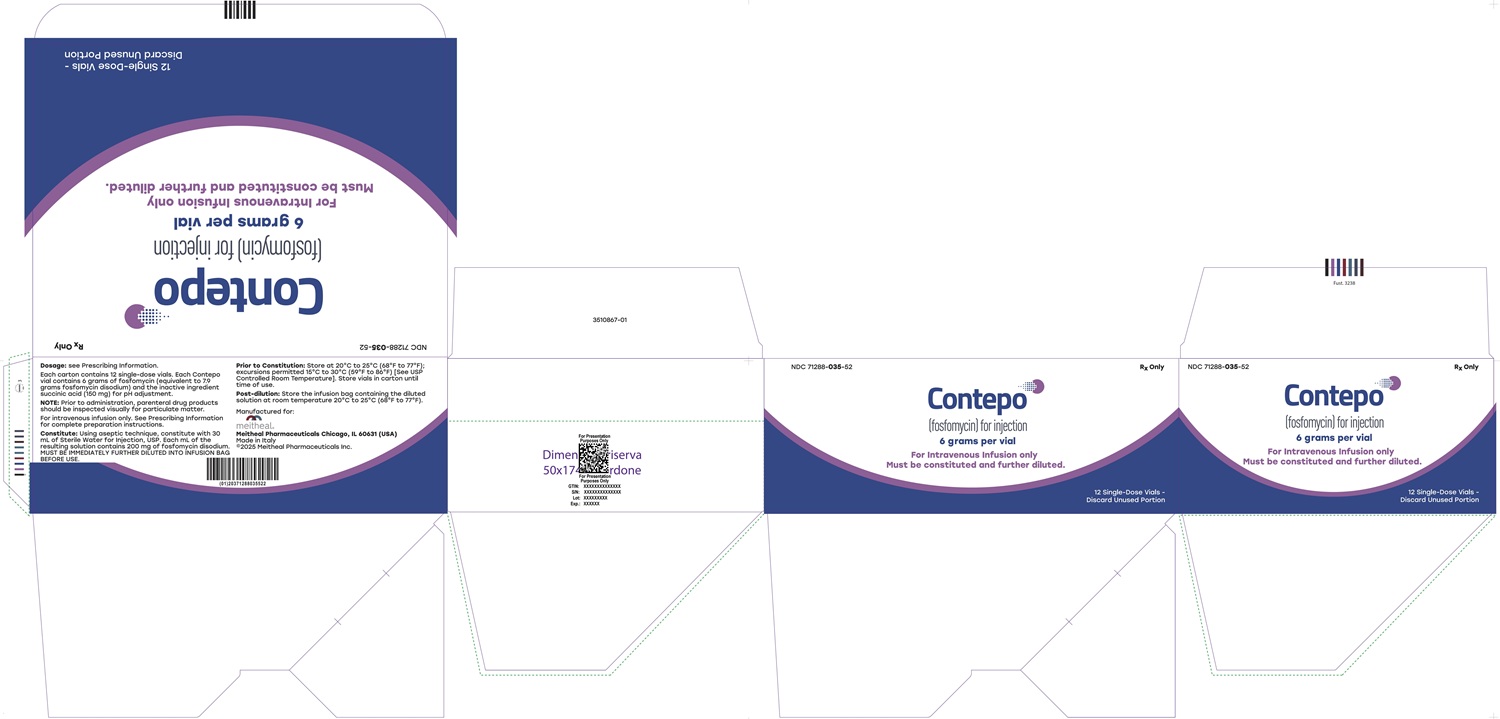 DRUG LABEL: Contepo
NDC: 71288-035 | Form: INJECTION, POWDER, FOR SOLUTION
Manufacturer: Meitheal Pharmaceuticals Inc.
Category: prescription | Type: HUMAN PRESCRIPTION DRUG LABEL
Date: 20251104

ACTIVE INGREDIENTS: FOSFOMYCIN SODIUM 6 g/1 1
INACTIVE INGREDIENTS: succinic acid

HIGHLIGHTS OF PRESCRIBING INFORMATION

These highlights do not include all the information needed to use CONTEPO safely and effectively. See full prescribing information for CONTEPO.
CONTEPO (fosfomycin) for injection, for intravenous use
Initial U.S. Approval: 1996

1 INDICATIONS AND USAGE

CONTEPO is an epoxide antibacterial indicated for the treatment of patients 18 years of age and older with complicated urinary tract infections (cUTI) including acute pyelonephritis caused by susceptible isolates of Escherichia coli and Klebsiella pneumoniae. (1.1)

Usage to Reduce Development of Drug-Resistant Bacteria

To reduce the development of drug-resistant bacteria and maintain the effectiveness of CONTEPO and other antibacterial drugs, CONTEPO should be used only to treat infections that are proven or strongly suspected to be caused by bacteria. (1.2)

2 DOSAGE AND ADMINISTRATION

- Administer CONTEPO, 6 grams every 8 hours by intravenous (IV) infusion over 1 hour for up to 14 days, in patients 18 years of age or older with an estimated creatinine clearance (CLcr) greater than 50 mL/min. (2.1)
- The recommended dosage in patients 18 years of age and older with an estimated CLcr of 50 mL/min or less is presented in the table below. (2.2)

Estimated CLcr (mL/min) a | Loading Doseb | Maintenance Dosageb
Estimated CLcr (mL/min) a | Loading Doseb | Dose | Frequency
41-50 | 6 grams | 4 grams | Every 8 hours
31-40 | 6 grams | 3 grams | Every 8 hours
21-30 | 6 grams | 5 grams | Every 24 hours
11-20 | 6 grams | 3 grams | Every 24 hours
aCLcr estimated using Cockcroft-Gault Equation.
bAll doses of CONTEPO are administered by intravenous infusion over 1 hour.

- Approximately 60% to 80% of the fosfomycin dose is cleared from the body by hemodialysis. Administer CONTEPO after hemodialysis on hemodialysis days. (2.2)

3 DOSAGE FORMS AND STRENGTHS

CONTEPO for Injection contains 6 grams of fosfomycin as a sterile powder in single-dose vials for reconstitution and further dilution. (3)

4 CONTRAINDICATIONS

CONTEPO is contraindicated in patients with known serious hypersensitivity to fosfomycin, or any of the excipients. (4)

5 WARNINGS AND PRECAUTIONS

- Serum Electrolyte Abnormalities: CONTEPO contains 1980 mg sodium in each vial. The high sodium load associated with the use of CONTEPO may result in changes in serum electrolytes, such as increased levels of sodium and decreased levels of potassium, calcium and phosphorus. A low-sodium diet is recommended during CONTEPO treatment. Monitor serum electrolyte levels and fluid status during CONTEPO treatment. Monitor signs and symptoms of edema, particularly in patients with cardiac insufficiency, renal impairment, cirrhosis, hypertension, hyperaldosteronism, hypernatremia or pulmonary edema. (5.1)
- QT Prolongation: CONTEPO has been shown to prolong the QT interval in some patients in the clinical trial. Avoid CONTEPO in patients with known prolongation of the QT interval or ventricular arrhythmias, including a history of torsade de pointes. (5.2, 7.1)
- Increased Transaminase Levels: Increase in alanine aminotransferase (ALT) and aspartate aminotransferase (AST) were reported in the clinical trial. Monitor hepatic enzymes during CONTEPO treatment. (5.3)
- Hypersensitivity Reactions: Reactions such as rash, urticaria and anaphylaxis were reported with the use of CONTEPO. Before initiating therapy with CONTEPO, it is important to inquire about previous hypersensitivity reactions to oral or parenteral fosfomycin. If an allergic reaction occurs, discontinue CONTEPO immediately. (5.4)
- Neutropenia Including Agranulocytosis: Neutropenia, including agranulocytosis, has occurred in patients receiving IV fosfomycin treatment. Monitor complete blood count during CONTEPO therapy. If such reactions occur, discontinue CONTEPO and institute appropriate treatment (5.5).
- Clostridioides difficile-Associated Diarrhea (CDAD): This has been reported with nearly all systemic antibacterial agents, including CONTEPO. Evaluate patients if diarrhea occurs. (5.6)

6 ADVERSE REACTIONS

Most common adverse reactions (incidence ≥2%) are transaminase elevations, hypokalemia, neutropenia, nausea, vomiting, diarrhea, hypocalcemia, hypernatremia, headache, and hypophosphatemia. (6.1)

To report SUSPECTED ADVERSE REACTIONS, contact Meitheal Pharmaceuticals Inc. at 1-844-824-8426 or FDA at 1-800-FDA-1088 or www.fda.gov/medwatch.

7 DRUG INTERACTIONS

Avoid co-administration of CONTEPO with drugs known to prolong the QT interval. (5.2, 7.1)

8 USE IN SPECIFIC POPULATIONS

Lactation: Breastfeeding not recommended during treatment and 24 hours after the last dose (8.2).

FULL PRESCRIBING INFORMATION

1 INDICATIONS AND USAGE

1.1 Complicated Urinary Tract Infections (cUTI), including Acute Pyelonephritis

CONTEPO is indicated for the treatment of patients 18 years and older with complicated urinary tract infections (cUTI), including acute pyelonephritis, caused by susceptible isolates of Escherichia coli and Klebsiella pneumoniae.

1.2 Usage to Reduce Development of Drug-Resistant Bacteria

To reduce the development of drug-resistant bacteria and maintain the effectiveness of CONTEPO and other antibacterial drugs, CONTEPO should be used only to treat infections that are proven or strongly suspected to be caused by susceptible bacteria. When culture and susceptibility information are available, they should be considered in selecting or modifying antibacterial therapy. In the absence of such data, local epidemiology and susceptibility patterns may contribute to the empiric selection of therapy.

2 DOSAGE AND ADMINISTRATION

2.1 Recommended Dosage

The recommended dosage of CONTEPO is 6 grams administered every 8 hours by intravenous (IV) infusion over 1 hour in patients 18 years of age or older with an estimated creatinine clearance (CLcr) greater than 50 mL/min. The duration of therapy is up to 14 days and should be guided by the severity of infection and the patient's clinical status. During treatment, different dosage recommendations may be required based on change in estimated CLcr [see Dosage and Administration (2.2)].

2.2 Recommended Dosage in Patients (18 Years of Age and Older) with Renal Impairment

The recommended dosage of CONTEPO in patients 18 years of age and older with an estimated CLcr of 50 mL/min or less is presented in Table 1. Monitor estimated CLcr and adjust the dosage of CONTEPO accordingly [see Warnings and Precautions (5.1), Use in Specific Populations (8.6) and Clinical Pharmacology (12.3)].

Table 1 Dosage of CONTEPO in Patients (18 Years of Age and Older) with Renal Impairment
Estimated CLcr (mL/min) a | Loading Doseb | Maintenance Dosageb
Estimated CLcr (mL/min) a | Loading Doseb | Dose | Frequency
41-50 | 6 grams | 4 grams | Every 8 hours
31-40 | 6 grams | 3 grams | Every 8 hours
21-30 | 6 grams | 5 grams | Every 24 hours
11-20 | 6 grams | 3 grams | Every 24 hours
a CLcr estimated by Cockcroft-Gault Equation.
bAll doses of CONTEPO are administered by IV infusion over 1 hour.

Approximately 60 to 80 % of the fosfomycin dose is cleared from the body by hemodialysis. Administer CONTEPO after hemodialysis on hemodialysis days.

2.3 Preparation of Diluted Solutions of CONTEPO

Preparation

CONTEPO is supplied as a dry powder in a single-dose vial that must be constituted and further diluted prior to intravenous infusion as described below. CONTEPO does not contain preservatives. Aseptic technique must be used for constitution and dilution prior to IV infusion.

1. Constitute the vial with 30 mL of Sterile Water for Injection, USP and gently mix to completely dissolve contents. A slight degree of warming occurs when the powder is dissolved. The constituted solution should appear clear and colorless. Parenteral drug products should be inspected visually for particulate matter and discoloration prior to administration, whenever solution and container permit. The constituted solution is not for direct injection and must be further diluted immediately with Sterile Water for Injection, USP [see Dosage and Administration (2.4)] before intravenous infusion.
2. To prepare the infusion solution, first remove 80 mL from a 250 mL intravenous bag of Sterile Water for Injection, USP for infusion so that it contains approximately 170 mL.
3. Then add the required volume of constituted solution to the infusion bag according to Table 2. Discard unused portion. The constituted and further diluted solution of CONTEPO has a pH of 7.4 to 7.8.

Table 2 Preparation of CONTEPO Doses
CONTEPO Dose | Volume to Withdraw from Constituted Vial | Volume of Final Infusion Bag (Approximate) | Final Infusion Concentration of CONTEPO (Approximate)
6 grams | 32.6 mL (Entire Contents) | 202 mL | 30 mg/mL
5 grams | 27 mL | 197 mL | 25 mg/mL
4 grams | 21.5 mL | 192 mL | 20 mg/mL
3 grams | 16 mL | 186 mL | 15 mg/mL

2.4 Stability of CONTEPO Solution in Intravenous Fluids

Because CONTEPO contains a high sodium content (1,980 mg per vial) [see Warnings and Precautions (5.2)], the infusion solution for dilution is Sterile Water for Injection, USP. After dilution, CONTEPO solution for administration is stable for 16 hours at room temperature (20°C to 25°C) at a concentration of 15 mg/mL to 30 mg/mL in Sterile Water for Injection, USP.

2.5 Drug Incompatibility

The compatibility of CONTEPO with other drugs and infusion solutions has not been established. CONTEPO should not be mixed or co-administered with solutions containing other drugs.

3 DOSAGE FORMS AND STRENGTHS

CONTEPO for Injection contains 6 grams of fosfomycin, and is supplied as a white or almost white, sterile powder in single-dose vials, for constitution and further dilution.

4 CONTRAINDICATIONS

CONTEPO is contraindicated in patients with known serious hypersensitivity to fosfomycin, or any of the excipients [see Warnings and Precautions (5.2)].

5 WARNINGS AND PRECAUTIONS

5.1 Serum Electrolyte Abnormalities

CONTEPO contains 1,980 mg of sodium in each vial. The high sodium load associated with the use of CONTEPO may result in changes in serum electrolytes, such as increased levels of serum sodium and decreased levels of potassium, calcium, and phosphorous. Electrolyte disturbances, such as hypokalemia and hypocalcemia, may potentiate cardiac effects, including QT prolongation [see Warnings and Precautions (5.2) and Clinical Pharmacology (12.2)].

In Trial 1, a comparator-controlled clinical trial in patients with cUTI, hypokalemia, hypernatremia, hypophosphatemia, and hypocalcemia occurred more frequently in CONTEPO-treated patients compared with piperacillin/tazobactam-treated patients [see Adverse Reactions (6.1)]. Hypokalemia with serum potassium less than 3.0 mEq/L and/or requiring potassium supplementation occurred in 9.9% of patients receiving CONTEPO and 1.7% of patients receiving piperacillin/tazobactam. Hypophosphatemia with serum phosphate concentrations less than 1.0 mg/dL occurred in 2.1% of patients receiving CONTEPO and none of the patients receiving piperacillin/tazobactam. Hypernatremia with serum sodium greater than 150 mEq/L occurred in 3.4% of patients receiving CONTEPO and 0.9% of patients receiving piperacillin/tazobactam. Hypocalcemia with corrected serum calcium less than 8.0 mg/dL occurred in 3.9% of patients receiving CONTEPO and 2.6% of patients receiving piperacillin/tazobactam.

A low-sodium diet is recommended during CONTEPO treatment. Minimize administration of drugs containing sodium. Monitor serum electrolyte levels (sodium, potassium, calcium, magnesium, and phosphorus) and fluid status during treatment with CONTEPO. Electrolyte supplementation may be necessary in some cases. Monitor for signs of edema, particularly in patients who should restrict their sodium intake or are prone to fluid overload (e.g., cardiac insufficiency, renal impairment, cirrhosis, hypertension, hyperaldosteronism, hypernatremia or pulmonary edema) [see Adverse Reactions (6.1)].

5.2 QT Prolongation

CONTEPO has been shown to prolong the QT interval in some patients. QT prolongation can lead to development of torsade de pointes-type ventricular tachycardia with the risk increasing as the degree of prolongation increases. In Trial 1, 3.6% of patients treated with CONTEPO had > 60 msec increase in QTcF interval from baseline and 1% of patients had QTcF > 480 msec. Torsade de pointes has been reported during postmarketing experience with fosfomycin [see Adverse Reactions (6.2)]. The risk of QT prolongation may increase in patients with electrolyte abnormalities (such as hypokalemia and hypocalcemia), patients with conditions that have potential to cause electrolyte imbalance (such as renal impairment), or patients taking other drugs affecting electrolyte balance or QT prolongation. Avoid CONTEPO in patients with known QT prolongation or ventricular arrhythmias, including a history of torsade de pointes. Monitor electrolytes during treatment with CONTEPO [see Warnings and Precautions (5.1), Drug Interactions (7.1) and Clinical Pharmacology (12.2)].

5.3 Increased Transaminase Levels

In Trial 1, increases in transaminases occurred more frequently in CONTEPO-treated patients compared to piperacillin/tazobactam-treated patients. Transaminases (Alanine Aminotransferase (ALT) or Aspartate Aminotransferase (AST) were elevated ≥ 3x upper limit of normal (ULN) in 10.3% of patients receiving CONTEPO and 4.8% of patients receiving piperacillin/tazobactam. Transaminase elevations were asymptomatic and reversible. No concurrent increases in serum bilirubin or alkaline phosphatase were observed. No patients met Hy's Law criteria, and no patients discontinued CONTEPO therapy because of treatment-related transaminase elevation [see Adverse Reactions (6.1)]. Monitor hepatic enzymes during CONTEPO treatment.

5.4 Hypersensitivity Reactions

CONTEPO is contraindicated in patients with known serious hypersensitivity to fosfomycin, or any of the excipients [see Contraindications (4)]. Hypersensitivity reactions, such as rash and urticaria, were reported in patients treated with CONTEPO in Trial 1. Anaphylaxis has been reported postmarketing [see Adverse Reactions (6.2)]. Before initiating therapy with CONTEPO, it is important to inquire about previous hypersensitivity reactions to oral or parenteral fosfomycin. If an allergic reaction to CONTEPO occurs, discontinue the drug immediately.

5.5 Neutropenia Including Agranulocytosis

Neutropenia has been reported in patients receiving IV fosfomycin therapy. In Trial 1, 6.4% of patients in the CONTEPO arm developed neutropenia (absolute neutrophil count less than 1500 cells/mm^3) as compared to 3.9% in the piperacillin/tazobactam comparator arm. In the post marketing setting, neutropenia cases progressing to agranulocytosis have been reported with IV fosfomycin therapy. Monitor complete blood counts during CONTEPO therapy particularly in patients with pre-existing conditions or patients receiving concomitant drugs that may predispose to bone marrow suppression. Discontinue CONTEPO if neutropenia occurs and consider alternative therapies.

5.6 Clostridioides difficile-Associated Diarrhea

Clostridioides difficile-associated diarrhea (CDAD) has been reported with use of nearly all systemic antibacterial agents, including CONTEPO, and may range in severity from mild to fatal colitis. Treatment with antibacterial agents alters the normal flora of the colon and may permit overgrowth of C. difficile.

C. difficile produces toxins A and B which contribute to the development of CDAD. CDAD must be considered in all patients who present with diarrhea following antibacterial use. Careful medical history is necessary because CDAD has been reported to occur more than 2 months after administration of antibacterial agents.

If CDAD is confirmed, discontinue antibacterials not directed against C. difficile, if possible. Manage fluid and electrolyte levels as appropriate, supplement protein intake, monitor antibacterial treatment of C. difficile, and institute surgical evaluation as clinically indicated.

5.7 Development of Drug-resistant Bacteria

Prescribing CONTEPO in the absence of a proven or strongly suspected bacterial infection indication is unlikely to provide benefit to the patient and increases the risk of the development of drug resistant bacteria [see Indications and Usage (1.2)].

6 ADVERSE REACTIONS

The following adverse reactions are discussed in greater detail in the Warnings and Precautions section:

- Serum Electrolyte Abnormalities [see Warnings and Precautions (5.1)]
- QT Prolongation [see Warnings and Precautions (5.2)]
- Increased Transaminase Levels [see Warnings and Precautions (5.3)]
- Hypersensitivity Reactions [see Warnings and Precautions (5.4)]
- Neutropenia Including Agranulocytosis [see Warnings and Precautions (5.5)]
- Clostridioides difficile-Associated Diarrhea [see Warnings and Precautions (5.6)]
- Development of Drug-Resistant Bacteria [see Warnings and Precautions (5.7)]

6.1 Clinical Trials Experience

Because clinical trials are conducted under widely varying conditions, adverse reaction rates observed in the clinical trials of a drug cannot be directly compared to rates in the clinical trials of another drug and may not reflect the rates observed in practice.

CONTEPO was evaluated in a comparator-controlled clinical trial (Trial 1) in patients with cUTI, including acute pyelonephritis, which included 233 patients treated with CONTEPO and 231 treated with comparator (piperacillin/tazobactam 4.5 g every 8 hours) for 7 days, allowing bacteremic patients to receive up to 14 days. No switch to oral antibacterial drugs was allowed. The median age of treated patients was 54 years (range 18-89 years) and 64% were female. All patients were white (100%). Patients (99%) were predominantly enrolled in Eastern Europe. Concomitant bacteremia was identified in 9% of patients at baseline.

Serious Adverse Reactions and Adverse Reactions Leading to Discontinuation

Serious adverse reactions occurred in 2.1% (5/233) CONTEPO and 2.6% (6/231) piperacillin/tazobactam-treated patients, respectively. Treatment was discontinued due to adverse reactions in 3% (7/233) of patients receiving CONTEPO and in 2.6% (7/231) of patients receiving piperacillin/tazobactam. The most common adverse reactions resulting in discontinuation of CONTEPO were gastrointestinal disorders (nausea, vomiting, and abdominal pain) in 1.3% (3/233) of patients. No deaths occurred in the clinical trial.

Common Adverse Reactions

Table 3 lists adverse reactions occurring in 2% or greater of patients receiving CONTEPO in Trial 1. These adverse reactions were reversible upon completion of therapy.

Table 3 Adverse Reactions Occurring in 2% or Greater of Patients with cUTI Receiving CONTEPO in Trial 1
Adverse Reaction
Adverse Reaction | CONTEPO N=233 % | Piperacillin/Tazobactam N=231 %
Gastrointestinal Disorders
Nausea | 4.3 | 1.3
Diarrhea | 3.9 | 4.8
Vomiting | 3.9 | 0.4
Laboratory Investigations
Transaminase elevations a | 10.3 | 4.8
Hypokalemia | 9.9 | 1.7
Hypophosphatemia | 2.1 | 0.0
Hypocalcemia | 3.9 | 2.6
Hypernatremia | 3.4 | 0.9
Blood and Lymphatic System Disorders
Neutropeniab | 6.4 | 3.9
Nervous System Disorders
Headache | 2.6 | 2.2
aTransaminase elevations include increased ALT and AST ≥3x ULN.
bNeutropenia includes absolute neutrophil count <1500 cells/mm^3

Adverse Reactions Occurring in < 2% of Patients Receiving CONTEPO in Trial 1:

Blood and lymphatic system disorders: anemia, thrombocytopenia

Cardiac disorders: atrial fibrillation, palpitations, tachycardia, heart failure

Ear and labyrinth disorders: hearing loss

Gastrointestinal disorders: constipation

General disorders and administration site conditions: asthenia, infusion site reactions, peripheral edema

Hepatobiliary disorders: hepatic steatosis, hepatomegaly

Infections and infestations: vaginal infection, vaginitis

Investigations: increase creatinine kinase

Metabolism and nutritional disorders: hyperglycemia

Nervous system disorders: dysgeusia, syncope

Respiratory, thoracic, and mediastinal disorders: dyspnea

Skin and subcutaneous disorders: urticaria, rash, pruritis

6.2 Postmarketing Experience

The following additional adverse reactions were not reported with CONTEPO-treated patients in Trial 1 but have been identified with the use of oral fosfomycin tromethamine or during use of intravenous fosfomycin sodium outside of the United States for various indications and dosing regimens. Because these reactions are reported voluntarily from a population of uncertain size, it is not always possible to reliably estimate their frequency or establish a causal relationship to drug exposure:

Blood and lymphatic system disorders: aplastic anemia, eosinophilia, agranulocytosis, leukopenia, pancytopenia

Cardiac disorders: torsade de pointes

Ear and labyrinth disorders: vertigo

Eye disorders: visual impairment

Gastrointestinal disorders: dyspepsia, C. difficile-associated diarrhea and colitis, toxic megacolon

Hepatobiliary disorders: alkaline phosphatase increased, cholestatic hepatitis, icterus, hepatic necrosis

Immune system disorders: anaphylaxis

Metabolism and nutrition disorders: decreased appetite

Nervous system disorders: cerebral edema, dizziness, optic neuritis

Psychiatric disorders: confusion

Respiratory, thoracic, and mediastinal disorders: asthma attack, pulmonary edema

Skin and subcutaneous tissue disorders: angioedema, facial edema

Vascular disorders: hypertension

7 DRUG INTERACTIONS

7.1 Drugs that prolong QT interval

Co-administration of CONTEPO with other drugs known to prolong the QT interval may increase the risk for ventricular arrhythmia. Avoid co-administration of CONTEPO with drugs known to prolong the QT interval, such as class IA or class III antiarrhythmic medications, tricyclic antidepressants, macrolides, and antipsychotics [see Warnings and Precautions (5.2)].

8 USE IN SPECIFIC POPULATIONS

8.1 Pregnancy

Risk Summary

Available data from observational studies and pharmacovigilance reports with fosfomycin use in pregnant women are insufficient to identify a drug-associated risk of major birth defects, miscarriage, or adverse maternal or fetal outcomes. Fosfomycin crosses the placental barrier. There are no animal data that meet current standards for nonclinical developmental toxicity studies. However, some reproductive toxicity data are available from published literature. Intravenous or intraperitoneal fosfomycin-sodium did not cause malformations in rabbits or rats, respectively, but showed evidence of fetotoxicity (see Data). The clinical relevance of these animal data is uncertain.

The background risk of major birth defects and miscarriage for the indicated population is unknown. All pregnancies have a background risk of birth defect, loss or other adverse outcomes. In the U.S. general population, the estimated background risk of major birth defect and miscarriage in clinically recognized pregnancies is 2% to 4% and 15% to 20%, respectively.

Data

Animal Data

Fosfomycin crosses the placenta in rats and rabbits. In rats administered intraperitoneal fosfomycin sodium on Days 7 to 17 of gestation (during organogenesis), there were increased numbers of dead or resorbed fetuses at 1500 mg/kg (approximately 0.8 times the recommended human dose of 18 g/day, based on body surface area comparisons), a dose associated with maternal toxicity . Rabbits were administered intravenous fosfomycin sodium on Days 6 to 18 of gestation (during organogenesis) at doses 800 mg/kg (approximately 0.9 times the recommended human dose). No malformations were observed in rabbits or rats after intravenous or intraperitoneal fosfomycin sodium, respectively.

In a pre- and post-natal developmental study in rats (dosed intraperitoneally with fosfomycin tromethamine between gestational day 6 and postnatal Day 21), no effects were observed in first-generation offspring at doses up to 1000 mg/kg, about 0.5 times the clinical dose, based on body surface area comparisons. Survival and postnatal body growth also were normal in the second-generation offspring at all doses.

8.2 Lactation

Risk Summary

Fosfomycin is present in human milk. There are no data on the effects of fosfomycin on the breastfed child or on milk production. Because of the potential for adverse reactions in a breastfed infant, advise patients not to breastfeed during treatment with CONTEPO and for 24 hours after the last dose.

8.4 Pediatric Use

Safety and effectiveness of CONTEPO in patients less than 18 years of age has not been established.

8.5 Geriatric Use

Of the 233 patients treated with CONTEPO in Trial 1, 32% (74/233) were 65 years of age and older, including 11.2% (26/233) who were 75 years of age and older. For patients included in the microbiological modified intent-to-treat (mMITT) population, lower overall success rates were observed for CONTEPO-treated and piperacillin/tazobactam-treated patients ≥ 65 years of age (53.6% and 43.9%, respectively) as compared to patients < 65 years (68.4% and 61.6%, respectively).

For patients ≥ 65 years of age, the incidence rate of adverse reactions was 39.2% (29/74) in CONTEPO-treated patients and 28.6% (22/77) in the piperacillin/tazobactam-treated patients. For patients <65 years of age, the incidence rate of adverse reactions was 43.4% (69/159) in CONTEPO-treated patients and 33.8% (52/154) in the piperacillin/tazobactam-treated patients.

Because elderly patients are more likely to have decreased cardiac and renal function, care should be taken in dose selection, and electrolytes, fluid status, and renal function should be monitored. Dosage adjustment in elderly patients should take into account renal function [see Dosage and Administration (2.2, 2.3, 2.4) and Clinical Pharmacology (12.3)].

8.6 Renal Impairment

Dosage adjustment is required for patients with estimated CLcr 50 mL/min or less. Monitor estimated CLcr and adjust the dosage of CONTEPO accordingly [see Dosage and Administration (2.2)].

In patients requiring hemodialysis, CONTEPO should be administered after hemodialysis on hemodialysis days [see Dosage and Administration (2.2), Clinical Pharmacology (12.3)].

8.7 Hepatic Impairment

Monitor patients with severe hepatic impairment closely for fluid overload and electrolyte abnormalities [see Warnings and Precautions (5.1), Clinical Pharmacology (12.3)].

10 OVERDOSAGE

To date, no cases of accidental overdose with clinically relevant intolerances have been reported. In the event of an overdose, the patient must be monitored and treated symptomatically. Fosfomycin is cleared from the body by hemodialysis, during which patients with end stage renal disease have an increased mean fosfomycin elimination half-life to approximately 4 hours.

11 DESCRIPTION

CONTEPO (fosfomycin) for injection, for intravenous use, contains fosfomycin disodium, an epoxide antibacterial drug.

Fosfomycin disodium is a powder with the chemical name of disodium [(2R,3S)-3-methyloxiran-2-yl]-dioxido-oxophosphorane, an empirical formula of C3H5Na2O4P and molecular weight of 182.

Figure 1 Chemical Structure of Fosfomycin Disodium

Each CONTEPO for Injection single-dose vial contains white to almost white sterile powder with 6 grams of fosfomycin (equivalent to 7.9 grams fosfomycin disodium) and the inactive ingredient succinic acid (150 mg) for pH adjustment. It is intended for constitution and further dilution prior to intravenous infusion . Each gram of fosfomycin disodium contains 330 mg of sodium (i.e., each vial contains 1,980 mg of sodium).

12 CLINICAL PHARMACOLOGY

12.1 Mechanism of Action

CONTEPO is an antibacterial drug [see Microbiology (12.4)].

12.2 Pharmacodynamics

The ratio of the unbound plasma fosfomycin AUC to MIC against the infecting organism has been shown to correlate with activity in animal models of infection.

Cardiac Electrophysiology

The effect of CONTEPO on 12-lead electrocardiogram parameters was evaluated in a Phase 1 randomized, placebo and positive controlled, double-blind, single-dose crossover study in 36 healthy adult subjects. At single doses of 6 grams and 12 grams (2 times the maximum single recommended dosage), CONTEPO demonstrated a dose dependent increase in QTcF. Mean placebo-corrected QTcF change from baseline was 8.3 msec (90% CI: 5.39 to 11.30) and 17.0 msec (90% CI: 14.06 to 20.01) for single doses of 6 grams and 12 grams, respectively, compared to 13.4 msec (90% CI: 10.48 to 16.39) observed with the active control, oral moxifloxacin. There were no subjects receiving CONTEPO with QTcF change from baseline greater than 60 msec or a QTcF greater than 480 msec [see Warnings and Precautions (5.2)]. A 1-hour CONTEPO infusion of the studied doses did not have a clinically meaningful effect on heart rate or on cardiac conduction, i.e., the PR and QRS interval.

12.3 Pharmacokinetics

The mean pharmacokinetic parameters of fosfomycin in healthy adults with normal renal function after single doses of 6 grams administered as 1-hour IV infusion are summarized along with additional pharmacokinetic information in Table 4.

Table 4 Exposure Parameter Estimates (Mean ± SD)a Following Single Dose of 6 grams Fosfomycin Administered as 1-hour IV Infusion in Healthy Adults with Normal Renal Function
Cmax (mcg/mL) | 228 ± 43
AUC 0-inf (mcg∙hr/mL) | 734 ± 134
Dose Proportionality | Fosfomycin Cmax and AUC0-inf increase proportionally with dose
Distribution
Volume of Distribution (L) | 27 ± 5.2
Protein Binding | Fosfomycin is not bound to plasma proteins
Elimination
Half-Life (h) | 2.8 ± 0.6
Total Clearance (L/h) | 8.5 ± 1.7
Metabolism | Fosfomycin is not metabolized.
Excretion | Urine: 70% of dose is excreted unchanged at 12 hours; 74-80% of dose is excreted unchanged at 48 hours
a Based on non-compartmental analysis of PK data

Specific Populations

No clinically significant differences in the pharmacokinetics of fosfomycin based on sex, body weight/body surface area, race/ethnicity or age (18 to 89 years of age, when adjusted for renal function) were identified.

Patients with Renal Impairment

Dosage adjustment is required for patients whose creatinine clearance is 50 mL/min or less [see Dosage and Administration (2.2), Use in Specific Populations (8.6)]. When fosfomycin is administered prior to hemodialysis in patients on periodic or chronic hemodialysis, 61-79% of the fosfomycin dose is removed.

Patients with Hepatic Impairment

CONTEPO is not metabolized through the liver. The effect of hepatic impairment on the pharmacokinetics of CONTEPO is unknown. Monitoring fluid overload and electrolyte abnormalities is recommended for patients with severe hepatic impairment [see Warnings and Precautions (5.1), Use in Specific Populations (8.7)].

Drug Interaction Studies

In Vitro Studies

Fosfomycin at clinically relevant concentrations does not inhibit CYP1A2, CYP2B6, CYP2C8, CYP2C9, CYP2C19, CYP2D6, and CYP3A4/5. Fosfomycin does not induce CYP1A2, CYP2B6, and CYP3A4. Fosfomycin is not a substrate for P-gp, BCRP, OATP1B1, OATP1B3, OAT1, OAT3, OCT2, MATE1 or MATE2-K. Fosfomycin inhibits MATE1 and MATE2-K with the observed IC50 values of 30.0 mM (4142 mcg/mL) and 56.4 mM (7787 mcg/mL), respectively. Fosfomycin does not inhibit P-gp, BCRP, OATP1B1, OATP1B3, OAT1, OAT3, OCT1, and OCT2.

12.4 Microbiology

Mechanism of Action

Fosfomycin is an epoxide antibacterial drug that disrupts bacterial cell wall synthesis by covalently binding and inhibiting phosphoenolpyruvate transferase (MurA), thereby blocking the synthesis of peptidoglycan. Fosfomycin is bactericidal against Enterobacterales. Transport of fosfomycin into the bacterial cell occurs via two different transport systems, glycerol-3-phosphate (GlpT) and/or hexose-6-phosphate (UhpT).

Resistance

Resistance to fosfomycin may occur by chromosomal mutations leading to alterations of bacterial transport systems and/or modification of the fosfomycin binding site in MurA (Cys115). Spontaneous mutations conferring various levels of fosfomycin resistance in E. coli and other Enterobacterales in vitro have been shown to occur in the structural transport genes (glpT and uhpT), transport regulatory genes (uhpA, uhpB, and uhpC) and genes involved in cAMP synthesis (cyaA, ptsI), all causing a decrease in fosfomycin uptake. Diminished activity of both transport systems is also evident when inactivation of cAMP-CRP occurs.

Plasmid-borne resistance mechanisms may result in enzymatic inactivation of fosfomycin by binding to glutathione, or by cleavage of the carbon-phosphorus-bond in the fosfomycin molecule. The enzymes responsible for this type of resistance are fosfomycin hydrolyzing enzymes (FosA, FosB, FosX) and fosfomycin kinases (FomA, FomB and FosC).

Resistance to fosfomycin due to spontaneous mutations occurs at frequencies between 10^-7 to 10^-9 for E. coli and 10^-5 to 10^-8 for K. pneumoniae at 4 times the fosfomycin Minimum Inhibitory Concentration (MIC).

There is no known cross-resistance to other antibacterial drug classes.

Interaction With Other Antimicrobials

In vitro studies have not demonstrated antagonism between CONTEPO and the following antibacterial drugs: amikacin, gentamicin, aztreonam, ceftazidime, ceftriaxone, piperacillin/tazobactam, meropenem, levofloxacin, tigecycline, minocycline, linezolid, rifampin, trimethoprim-sulfamethoxazole, vancomycin, penicillin and colistin. The clinical significance of these findings is unknown.

Animal Infection Models

Fosfomycin demonstrated activity in neutropenic thigh infection models caused by either E. coli (KPC and NDM producing) or K. pneumoniae (KPC and VIM producing) isolates.

Antimicrobial Activity

CONTEPO has been shown to be active against most isolates of the following microorganisms, both in vitro and in clinical infections [see Indications and Usage (1.1)].

Aerobic bacteria

Gram-negative bacteria

Escherichia coli

Klebsiella pneumoniae

The following in vitro data are available, but their clinical significance is unknown. At least 90 percent of the following bacteria exhibit an in vitro minimum inhibitory concentration (MIC) less than or equal to the susceptible breakpoint for CONTEPO against isolates of similar genus or organism group. However, the efficacy of CONTEPO in treating clinical infections caused by these bacteria has not been established in adequate and well-controlled clinical trials.

Aerobic bacteria

Gram-negative bacteria

Citrobacter koseri

Enterobacter aerogenes

Klebsiella oxytoca

Proteus mirabilis

Serratia marcescens

Susceptibility Testing

For specific information regarding susceptibility test interpretive criteria, and associated test methods and quality control standards recognized by FDA for this drug, please see: https://www.fda.gov/STIC.

13 NONCLINICAL TOXICOLOGY

13.1 Carcinogenesis, Mutagenesis, Impairment of Fertility

Carcinogenesis

Long-term carcinogenicity studies have not been conducted with fosfomycin.

Mutagenesis

Fosfomycin did not show evidence of mutagenic activity in standard tests that included bacterial reverse mutation assay, chromosomal aberration assay with Chinese hamster lung fibroblast cells and human peripheral blood lymphocytes, and the mouse bone marrow micronucleus assay.

Impairment of Fertility

In a fertility study, male and female rats were dosed intraperitoneally with fosfomycin disodium (for 7 or 14 days, respectively, before mating, for 14 days during cohabitation, and in mated females up to gestation day 7 at doses of 125, 250, 750 or 1500 mg/kg. Maternal toxicity (mortality) was observed at the 1500 mg/kg dose (about 0.8 times the clinical dose based on body surface area comparisons) along with increases in the number of dead or resorbed fetuses and a reduction in the number of live fetuses. There were no effects on fertility at 750 mg/kg (approximately 0.4 times the clinical dose).

14 CLINICAL STUDIES

14.1 Complicated Urinary Tract Infections, Including Acute Pyelonephritis

A total of 464 adults hospitalized with cUTI (including acute pyelonephritis) were randomized and received study medications in a multinational, double-blind study (Trial 1, NCT02753946) comparing CONTEPO 6 g intravenously every 8 hours to piperacillin/tazobactam 4.5 g intravenously every 8 hours for 7 days of therapy. Treatment was allowed for up to 14 days in bacteremic patients. The study did not include a switch to oral antibacterial drugs.

The microbiological modified intent-to-treat (mMITT) population included all patients who received study medication and had at least 1 baseline uropathogen, excluding patients with organisms resistant to study drugs at baseline. This population consisted of 339 patients with cUTI, including 184 patients (54%) with acute pyelonephritis. The median age was 53 years and 64% were female. Concomitant bacteremia was identified in 9% of patients at baseline, and 32% of patients met 2 or more systemic inflammatory response syndrome (SIRS) criteria at baseline.

Overall success was defined as clinical cure plus microbiological eradication (baseline uropathogens with growth in urine ≥10^5 CFU/mL were reduced to <10^4 CFU/mL) at the test-of-cure (TOC) visit, 19 (+2) days after randomization. CONTEPO demonstrated efficacy with regard to the overall response at the TOC visit in the mMITT population (Table 5). A sensitivity analysis for overall success at the TOC visit using a threshold of 10^3 CFU/ml for microbiological eradication demonstrated similar efficacy results.

In the mMITT population, the overall success rates at TOC in patients with concurrent bacteremia were 9/19 (47.4%) for CONTEPO-treated patients and 5/13 (38.5%) in the piperacillin/tazobactam-treated patients.

Overall response rates at the TOC visit by pathogen in the mMITT population is presented in Table 6.

Table 5 Overall Response Rates at Test-of-Cure Visit in cUTI Patients in Trial 1 (mMITT Population)
Response ^1 | CONTEPO^2 n/N (%) | Piperacillin/ Tazobactam^3 n/N (%) | Treatment Difference (95% CI)
Overall success | 108/170 (63.5) | 94/169 (55.6) | 7.9 (-3.1, 18.9)
Clinical cure | 154/170 (90.6) | 155/169 (91.7) | -1.1 (-7.8, 5.5)
Microbiological eradication | 110/170 (64.7) | 97/169 (57.4) | 7.3 (-3.6, 18.3)
^1 Patients with an organism resistant to study drugs at baseline were to be excluded. All of the patients excluded
(14 in CONTEPO arm, 9 in piperacillin/tazobactam arm) had an organism resistant to piperacillin/tazobactam.
^2 CONTEPO 6 g intravenously every 8 hours
^3 Piperacillin/tazobactam 4.5 g every 8 hours

Table 6 Overall Response Rates at Test-of-Cure Visit by Baseline Pathogen in cUTI Patients in Trial 1 (mMITT Population)
Pathogen^1 | CONTEPO n/N (%) | Piperacillin/ Tazobactam n/N (%)
Escherichia coli | 87/130 (66.9) | 75/130 (57.7)
Klebsiella pneumoniae | 8/18 (44.4) | 11/20 (55.0)
^1 Patients with an organism resistant to piperacillin/tazobactam at baseline were excluded

16 HOW SUPPLIED/STORAGE AND HANDLING

How Supplied

CONTEPO for injection is supplied as a white to almost white sterile powder containing 6 grams of fosfomycin in a single-dose vial. Each gram of fosfomycin disodium contains 330 mg of sodium (i.e., each vial contains 1,980 mg of sodium).

CONTEPO is supplied in a clear Type I glass single-dose vial (NDC 71288-035-51) with a rubber closure and a twist-off cap. Twelve (12) vials are supplied in each carton (NDC 71288-035-52).

Storage and Handling

Store CONTEPO vials at 20°C to 25°C (68°F to 77°F); excursions permitted to 15°C to 30°C (59°F to 86°F) [See USP Controlled Room Temperature]. Store CONTEPO in the carton until time of use [see Dosage and Administration (2.4)].

17 PATIENT COUNSELING INFORMATION

Electrolyte Abnormalities

Advise patients that a low sodium diet is recommended during CONTEPO treatment because the high sodium load (each vial of CONTEPO contains 1,980 mg sodium) may cause changes in electrolytes or increased edema [see Warnings and Precautions (5.1)]. Blood tests to monitor electrolytes will be required. If peripheral edema develops, tell the patient to contact their health care provider.

Serious Allergic Reactions

Advise patients that allergic reactions, including serious allergic reactions, could occur and that serious reactions require immediate treatment. Ask patient about any previous hypersensitivity reactions to CONTEPO, fosfomycin or other allergens [see Warnings and Precautions (5.2)].

Potentially Serious Diarrhea

Advise patients that diarrhea is a common problem caused by antibacterial drugs, including CONTEPO. Sometimes, frequent watery or bloody diarrhea may occur and may be a sign of a more serious intestinal infection. If severe watery or bloody diarrhea develops, tell patient to contact his or her healthcare provider [see Warnings and Precautions (5.6)].

Antibacterial Resistance

Patients should be counseled that antibacterial drugs including CONTEPO should only be used to treat bacterial infections. They do not treat viral infections (e.g. the common cold). When CONTEPO is prescribed to treat a bacterial infection, patients should be told that although it is common to feel better early in the course of therapy, the medication should be taken exactly as directed. Skipping doses or not completing the full course of therapy may (1) decrease the effectiveness of the immediate treatment and (2) increase the likelihood that bacteria will develop resistance and will not be treatable by CONTEPO or other antibacterial drugs in the future [see Warnings and Precautions (5.7)].

Lactation

Advise females not to breastfeed during treatment with CONTEPO and for 24 hours after the final dose [see Use in Specific Populations (8.2)].

Manufactured for Meitheal Pharmaceuticals
Chicago, IL 60631 (USA)
Made in Italy
©2025 Meitheal Pharmaceuticals Inc.

CONTEPO is a trademark of Meitheal Pharmaceuticals, Inc.
All rights reserved

3510868-02

PRINCIPAL DISPLAY PANEL - CONTEPO 6 grams per vial Container Label

NDC 71288-035-51

Rx Only

Contepo

(fosfomycin) for injection

6 grams per vial

For Intravenous Infusion only

Must be constituted and further diluted.

Single-Dose Vial - Discard Unused Portion

PRINCIPAL DISPLAY PANEL - CONTEPO 6 grams per vial Carton Label

NDC 71288-035-52

Rx Only

Contepo

(fosfomycin) for injection

6 grams per vial

For Intravenous Infusion only

Must be constituted and further diluted.

12 Single-Dose Vials -

Discard Unused Portion